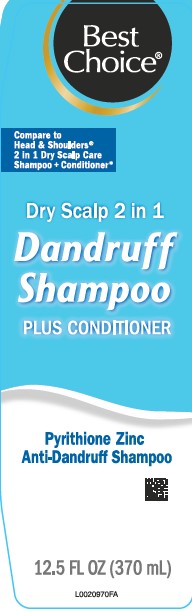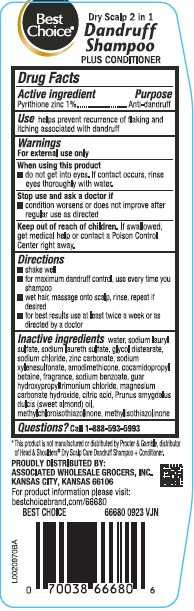 DRUG LABEL: Dry Scalp Care
NDC: 63941-296 | Form: SHAMPOO
Manufacturer: Valu Merchandisers Company
Category: otc | Type: HUMAN OTC DRUG LABEL
Date: 20260216

ACTIVE INGREDIENTS: PYRITHIONE ZINC 10 mg/1 mL
INACTIVE INGREDIENTS: WATER; SODIUM LAURYL SULFATE; SODIUM LAURETH SULFATE; GLYCOL DISTEARATE; SODIUM CHLORIDE; ZINC CARBONATE; SODIUM XYLENESULFONATE; AMODIMETHICONE (800 CST); COCAMIDOPROPYL BETAINE; SODIUM BENZOATE; GUAR HYDROXYPROPYLTRIMONIUM CHLORIDE (1.7 SUBSTITUENTS PER SACCHARIDE); MAGNESIUM CARBONATE HYDROXIDE; CITRIC ACID MONOHYDRATE; ALMOND OIL; METHYLCHLOROISOTHIAZOLINONE; METHYLISOTHIAZOLINONE

Best Choice 296.007-296AT-AW
Dandruff Shampoo, Dry Scalp 2 in 1

Claims

Best Choice®

Dry Scalp 2 in 1

Dandruff Shampoo

Plus Conditioner

Active ingredient

Pyrithione zinc 1%

Purpose

Anti-dandruff

Use

Helps prevent recurrence flaking and itching associated with dandruff

Warnings

For external use only

Stop use and ask a doctor if

condition worsens or does not improve after regular use as directed

keep out of reach of children.

If swallowed, get medical help or contact a Poison Control Center right away.

Directions

- shake well
- for maximum dandruff control, use every time you shampoo
- wet hair, massage onto scalp, rinse, repeat if desired
- for best results use at least twice a week or as directed by a doctor

Inactive ingredients

water, sodium lauryl sulfate, sodium laureth sulfate, glycol distearate, sodium chloride, zinc carbonate, sodium xylenesulfonate, amodimethicone, cocamidopropyl betaine, fragrance, sodium benzoate, guar hydroxypropyltrimonium chloride, magnesium carbonate hydroxide, citric acid, Prunus amygdalus dulcis (sweet almond) oil, methylchloroisothiazolinone, methylisothiazolinone

Disclaimer

*This product is not manufactured or distributed by Procter & Gamble, distributor of Head & Shoulders® Dry Scalp Care Dandruff Shampoo + Conditioner.

Adverse Reactions section

PROUDLY DISTRIBUTED BY:

ASSOCIATED WHOLESALE GROCERS, INC.

KANSAS CITY, KANSAS 66106

For product information please visit:

bestchoicebrand.com/66680

BEST CHOICE 66680 0923 VJN

Principal display panel

Best Choice®

Compare to Head & Shoulders® 2 in 1 Dry Scalp Care Shampoo + Conditioner*

Dry Scalp 2 in 1

Dandruff Shampoo

PLUS CONDITIONER

Pyrithone Zinc

Anti-Dandruff Shampoo

12.5 FL OZ (370 mL)